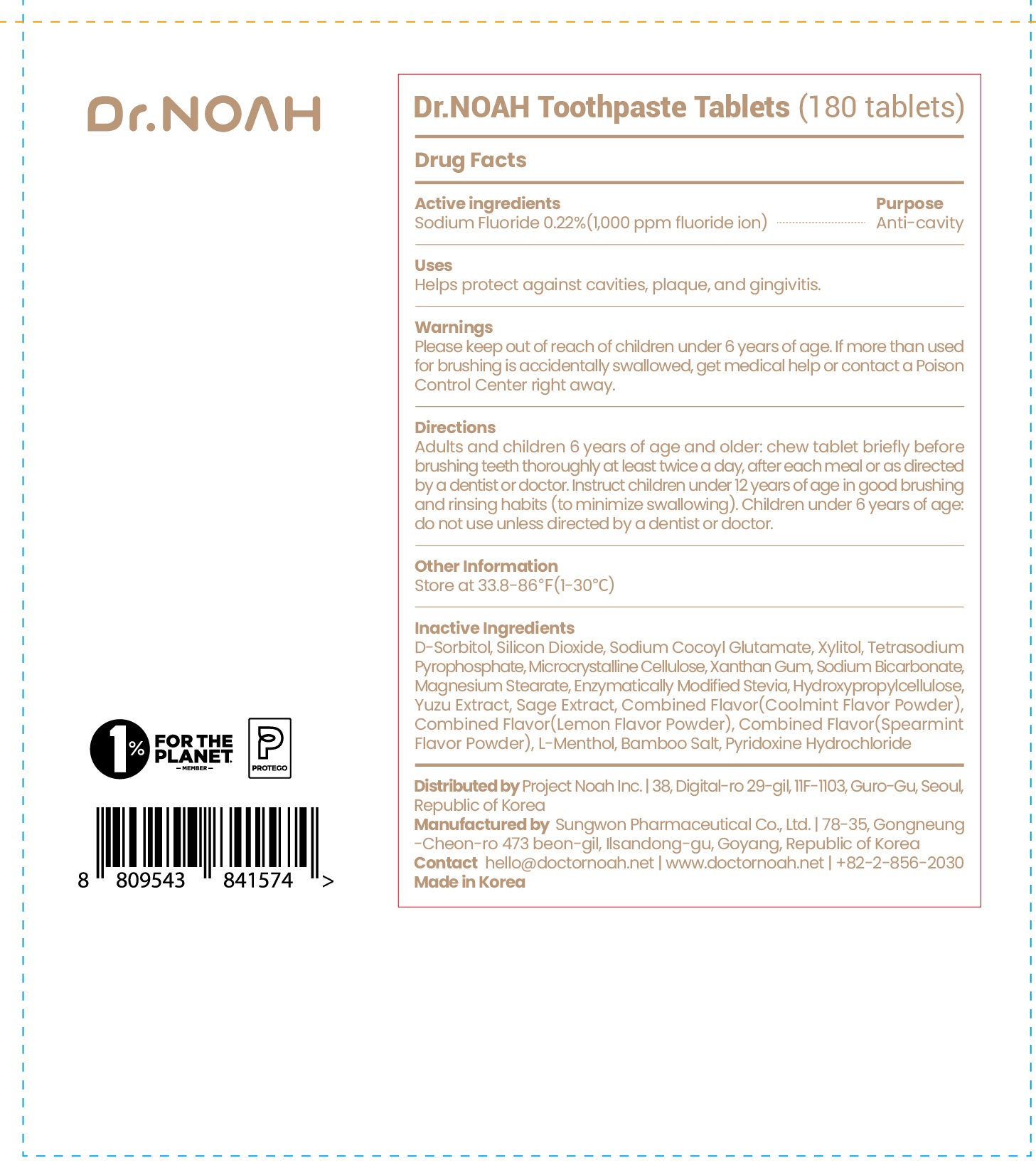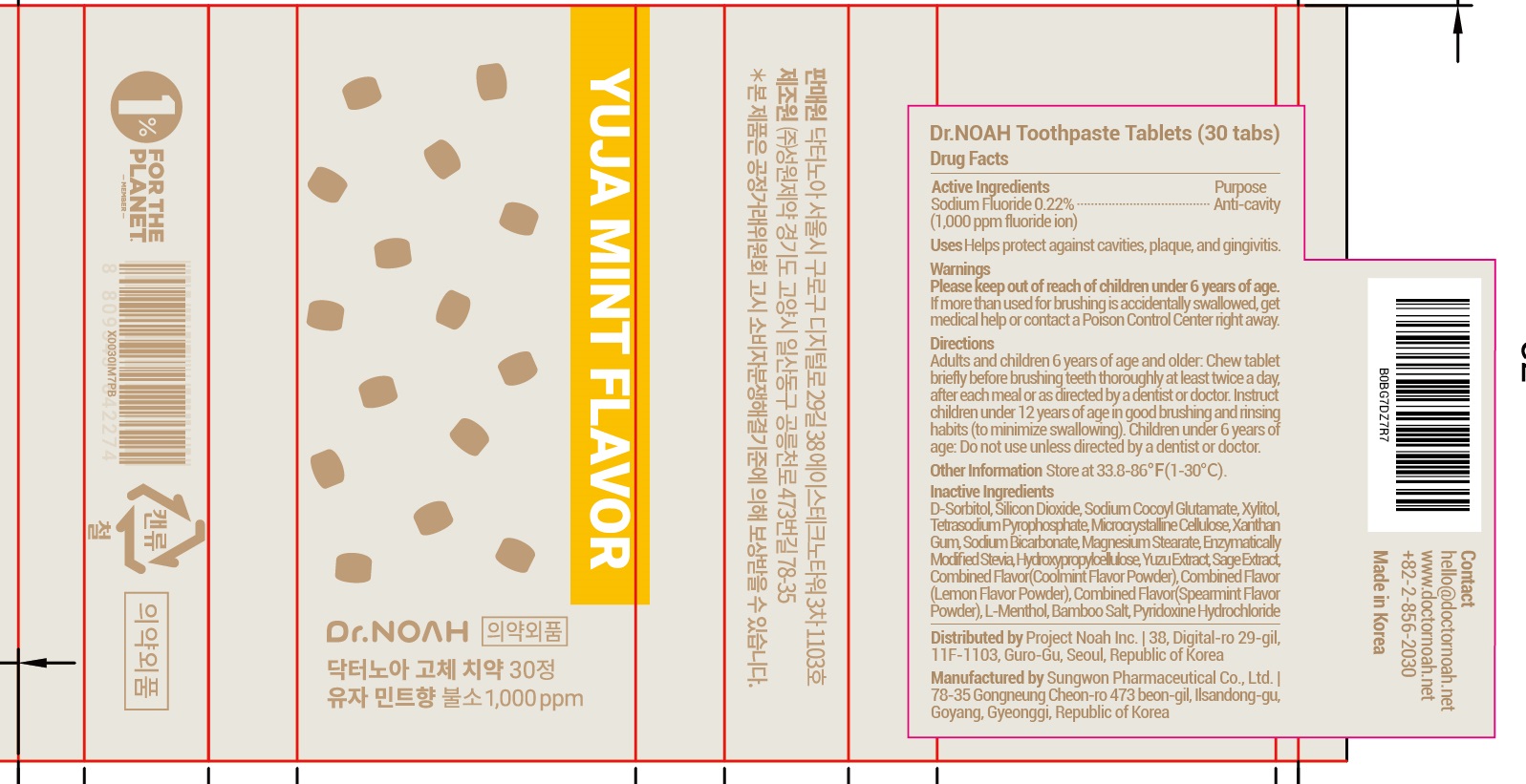 DRUG LABEL: Dr.NOAH Toothpaste Tablets
NDC: 82989-030 | Form: PASTE, DENTIFRICE
Manufacturer: Project Noah Inc.
Category: otc | Type: HUMAN OTC DRUG LABEL
Date: 20221013

ACTIVE INGREDIENTS: Sodium Fluoride 0.22 g/100 1
INACTIVE INGREDIENTS: SORBITOL; Silicon Dioxide; Sodium Cocoyl Glutamate

ACTIVE INGREDIENT

Sodium Fluoride 0.22%(1,000 ppm fluoride ion)

PURPOSE

Anti-cavity

Uses

■ Helps protect against cavities, plaque, and gingivitis.

Warnings

Please keep out of reach of children under 6 years of age. If more than used for brushing is accidentally swallowed, get medical help or contact a Poison Control Center right away.

keep out of reach of children under 6 years of age

Directions

■ Adults and children 6 years of age and older: Chew tablet briefly before brushing teeth thoroughly at least twice a day, after each meal or as directed by a dentist or doctor. Instruct children under 12 years of age in good brushing and rinsing habits (to minimize swallowing). Children under 6 years of age: Do not use unless directed by a dentist or doctor.

Other Information

■ Store at 33.8-86℉(1-30°C)

Inactive ingredients

D-Sorbitol, Silicon Dioxide, Sodium Cocoyl Glutamate, Xylitol, Tetrasodium Pyrophosphate, Microcrystalline Cellulose, Xanthan Gum, Sodium Bicarbonate, Magnesium Stearate, Enzymatically Modified Stevia, Hydroxypropylcellulose, Yuzu Extract, Sage Extract, Combined Flavor(Coolmint Flavor Powder), Combined Flavor(Lemon Flavor Powder), Combined Flavor(Spearmint Flavor Powder), L-Menthol, Bamboo Salt, Pyridoxine Hydrochloride